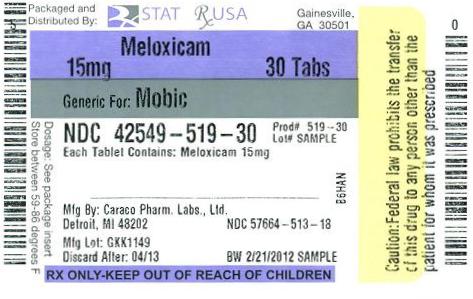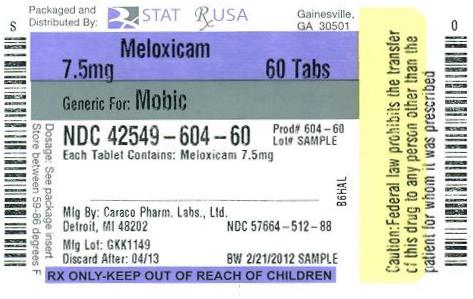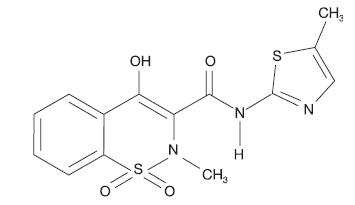 DRUG LABEL: Meloxicam
NDC: 42549-604 | Form: TABLET
Manufacturer: STAT Rx USA LLC
Category: prescription | Type: HUMAN PRESCRIPTION DRUG LABEL
Date: 20120223

ACTIVE INGREDIENTS: MELOXICAM 7.5 mg/1 1
INACTIVE INGREDIENTS: COLLOIDAL SILICON DIOXIDE; CROSPOVIDONE; LACTOSE; LACTOSE MONOHYDRATE; MAGNESIUM STEARATE; CELLULOSE, MICROCRYSTALLINE; POVIDONE; TRISODIUM CITRATE DIHYDRATE

Meloxicam

WARNING

Cardiovascular Risk

- NSAIDs may cause an increased risk of serious cardiovascular thrombotic events, myocardial infarction, and stroke, which can be fatal. This risk may increase with duration of use. Patients with cardiovascular disease or risk factors for cardiovascular disease may be at greater risk (see WARNINGS and CLINICAL TRIALS).
- Meloxicam tablet is contraindicated for the treatment of peri-operative pain in the setting of coronary artery bypass graft (CABG) surgery (see WARNINGS).

Gastrointestinal Risk

- NSAIDs cause an increased risk of serious gastrointestinal adverse events including bleeding, ulceration, and perforation of the stomach or intestines, which can be fatal. These events can occur at any time during use and without warning symptoms. Elderly patients are at greater risk for serious gastrointestinal events (see WARNINGS).

DESCRIPTION

Meloxicam, an oxicam derivative, is a member of the enolic acid group of nonsteroidal anti-inflammatory drugs (NSAIDs). Each tablet contains 7.5 mg or 15 mg meloxicam for oral administration. Meloxicam is chemically designated as 4-hydroxy-2-methyl-N-(5-methyl-2-thiazolyl)-2H-1,2-benzothiazine-3-carboxamide-1,1-dioxide. The molecular weight is 351.4. Its empirical formula is C14H13N3O4S2 and it has the following structural formula.

Meloxicam is a pastel yellow solid, practically insoluble in water, with higher solubility observed in strong acids and bases. It is very slightly soluble in methanol. Meloxicam has an apparent partition coefficient (log P)app = 0.1 in n-octanol/buffer pH 7.4. Meloxicam has pKa values of 1.1 and 4.2.

Meloxicam is available as a tablet for oral administration containing 7.5 mg or 15 mg meloxicam.

The inactive ingredients in Meloxicam tablets include: colloidal silicon dioxide, crospovidone, lactose monohydrate, magnesium stearate, microcrystalline cellulose, povidone and sodium citrate dihydrate.

CLINICAL PHARMACOLOGY

Mechanism of Action

Meloxicam is a nonsteroidal anti-inflammatory drug (NSAID) that exhibits anti-inflammatory, analgesic, and antipyretic activities in animal models. The mechanism of action of meloxicam, like that of other NSAIDs, may be related to prostaglandin synthetase (cyclo-oxygenase) inhibition.

Pharmacokinetics

Absorption

The absolute bioavailability of meloxicam capsules was 89% following a single oral dose of 30 mg compared with 30 mg IV bolus injection. Following single intravenous doses, dose-proportional pharmacokinetics were shown in the range of 5 mg to 60 mg. After multiple oral doses the pharmacokinetics of meloxicam capsules were dose-proportional over the range of 7.5 mg to 15 mg. Mean Cmax was achieved within four to five hours after a 7.5 mg meloxicam tablet was taken under fasted conditions, indicating a prolonged drug absorption. With multiple dosing, steady state concentrations were reached by Day 5. A second meloxicam concentration peak occurs around 12 to 14 hours post-dose suggesting biliary recycling.

Table 1 Single Dose and Steady State Pharmacokinetic Parameters for Oral 7.5 mg and 15 mg Meloxicam (Mean and % CV)^1
 | Steady State |  |  | Single Dose
Pharmacokinetic Parameters (% CV) | Healthy male adults (Fed)^2 | Elderly males (Fed)^2 | Elderly females (Fed)^2 | Renal failure (Fasted) | Hepatic insufficiency (Fasted)
Pharmacokinetic Parameters (% CV) | 7.5 mg^3 tablets | 15 mg capsules | 15 mg capsules | 15 mg capsules | 15 mg capsules
N | 18 | 5 | 8 | 12 | 12
Cmax [μg/mL] | 1.05 (20) | 2.3 (59) | 3.2 (24) | 0.59 (36) | 0.84 (29)
Tmax [h] | 4.9 (8) | 5 (12) | 6 (27) | 4 (65) | 10 (87)
t1/2 [h] | 20.1 (29) | 21 (34) | 24 (34) | 18 (46) | 16 (29)
CL/f [mL/min] | 8.8 (29) | 9.9 (76) | 5.1 (22) | 19 (43) | 11 (44)
Vz/f^4 [L] | 14.7 (32) | 15 (42) | 10 (30) | 26 (44) | 14 (29)
^1The parameter values in the Table are from various studies
^2not under high fat conditions
^3Meloxicam tablets
^4Vz/f =Dose/(AUC•Kel)

Food and Antacid Effects

Administration of meloxicam capsules following a high fat breakfast (75 g of fat) resulted in mean peak drug levels (i.e., Cmax) being increased by approximately 22% while the extent of absorption (AUC) was unchanged. The time to maximum concentration (Tmax) was achieved between 5 and 6 hours. No pharmacokinetic interaction was detected with concomitant administration of antacids. Based on these results, meloxicam tablets can be administered without regard to timing of meals or concomitant administration of antacids.

Distribution

The mean volume of distribution (Vss) of meloxicam is approximately 10 L. Meloxicam is ~ 99.4% bound to human plasma proteins (primarily albumin) within the therapeutic dose range. The fraction of protein binding is independent of drug concentration, over the clinically relevant concentration range, but decreases to ~ 99% in patients with renal disease. Meloxicam penetration into human red blood cells, after oral dosing, is less than 10%. Following a radiolabeled dose, over 90% of the radioactivity detected in the plasma was present as unchanged meloxicam.

Meloxicam concentrations in synovial fluid, after a single oral dose, range from 40% to 50% of those in plasma. The free fraction in synovial fluid is 2.5 times higher than in plasma, due to the lower albumin content in synovial fluid as compared to plasma. The significance of this penetration is unknown.

Metabolism

Meloxicam is almost completely metabolized to four pharmacologically inactive metabolites. The major metabolite, 5'-carboxy meloxicam (60% of dose), from P-450 mediated metabolism was formed by oxidation of an intermediate metabolite 5'-hydroxymethyl meloxicam which is also excreted to a lesser extent (9% of dose). In vitro studies indicate that cytochrome P-450 2C9 plays an important role in this metabolic pathway with a minor contribution of the CYP 3A4 isozyme. Patients’ peroxidase activity is probably responsible for the other two metabolites which account for 16% and 4% of the administered dose, respectively.

Excretion

Meloxicam excretion is predominantly in the form of metabolites, and occurs to equal extents in the urine and feces. Only traces of the unchanged parent compound are excreted in the urine (0.2%) and feces (1.6%). The extent of the urinary excretion was confirmed for unlabeled multiple 7.5 mg doses: 0.5%, 6% and 13% of the dose were found in urine in the form of meloxicam, and the 5'-hydroxymethyl and 5'-carboxy metabolites, respectively. There is significant biliary and/or enteral secretion of the drug. This was demonstrated when oral administration of cholestyramine following a single IV dose of meloxicam decreased the AUC of meloxicam by 50%.

The mean elimination half-life (t1/2) ranges from 15 hours to 20 hours. The elimination half-life is constant across dose levels indicating linear metabolism within the therapeutic dose range. Plasma clearance ranges from 7 to 9 mL/min.

Special Populations

Geriatric

Elderly males (≥ 65 years of age) exhibited meloxicam plasma concentrations and steady state pharmacokinetics similar to young males. Elderly females (≥ 65 years of age) had a 47% higher AUCss and 32% higher Cmax,ss as compared to younger females (≤ 55 years of age) after body weight normalization. Despite the increased total concentrations in the elderly females, the adverse event profile was comparable for both elderly patient populations. A smaller free fraction was found in elderly female patients in comparison to elderly male patients.

Gender

Young females exhibited slightly lower plasma concentrations relative to young males. After single doses of 7.5 mg meloxicam, the mean elimination half-life was 19.5 hours for the female group as compared to 23.4 hours for the male group. At steady state, the data were similar (17.9 hours vs. 21.4 hours). This pharmacokinetic difference due to gender is likely to be of little clinical importance. There was linearity of pharmacokinetics and no appreciable difference in the Cmax or Tmax across genders.

Hepatic Insufficiency

Following a single 15 mg dose of meloxicam there was no marked difference in plasma concentrations in subjects with mild (Child-Pugh Class I) and moderate (Child-Pugh Class II) hepatic impairment compared to healthy volunteers. Protein binding of meloxicam was not affected by hepatic insufficiency. No dose adjustment is necessary in mild to moderate hepatic insufficiency. Patients with severe hepatic impairment (Child-Pugh Class III) have not been adequately studied.

Renal Insufficiency

Meloxicam pharmacokinetics have been investigated in subjects with different degrees of renal insufficiency. Total drug plasma concentrations decreased with the degree of renal impairment while free AUC values were similar. Total clearance of meloxicam increased in these patients probably due to the increase in free fraction leading to an increased metabolic clearance. There is no need for dose adjustment in patients with mild to moderate renal failure (CrCL >15 mL/min). Patients with severe renal insufficiency have not been adequately studied. The use of meloxicam tablets in subjects with severe renal impairment is not recommended (see WARNINGS, Advanced Renal Disease).

Hemodialysis

Following a single dose of meloxicam, the free Cmax plasma concentrations were higher in patients with renal failure on chronic hemodialysis (1% free fraction) in comparison to healthy volunteers (0.3% free fraction). Hemodialysis did not lower the total drug concentration in plasma; therefore, additional doses are not necessary after hemodialysis. Meloxicam is not dialyzable.

CLINICAL TRIALS

Osteoarthritis and Rheumatoid Arthritis

The use of meloxicam for the treatment of the signs and symptoms of osteoarthritis of the knee and hip was evaluated in a 12-week double-blind controlled trial. Meloxicam (3.75 mg, 7.5 mg and 15 mg daily) was compared to placebo. The four primary endpoints were investigator's global assessment, patient global assessment, patient pain assessment, and total WOMAC score (a self-administered questionnaire addressing pain, function and stiffness). Patients on meloxicam 7.5 mg daily and meloxicam 15 mg daily showed significant improvement in each of these endpoints compared with placebo.

The use of meloxicam for the management of signs and symptoms of osteoarthritis was evaluated in six double-blind, active-controlled trials outside the U.S. ranging from 4 weeks to 6 months duration. In these trials, the efficacy of meloxicam, in doses of 7.5 mg/day and 15 mg/day, was comparable to piroxicam 20 mg/day and diclofenac SR 100 mg/day and consistent with the efficacy seen in the U.S. trial.

The use of meloxicam for the treatment of the signs and symptoms of rheumatoid arthritis was evaluated in a 12-week double-blind, controlled multinational trial. Meloxicam (7.5 mg, 15 mg and 22.5 mg daily) was compared to placebo. The primary endpoint in this study was the ACR20 response rate, a composite measure of clinical, laboratory and functional measures of RA response. Patients receiving meloxicam 7.5 mg and 15 mg daily showed significant improvement in the primary endpoint compared with placebo. No incremental benefit was observed with the 22.5 mg dose compared to the 15 mg dose.

Higher doses of meloxicam (22.5 mg and greater) have been associated with an increased risk of serious GI events; therefore the daily dose of meloxicam should not exceed 15 mg.

INDICATIONS AND USAGE

Carefully consider the potential benefits and risks of meloxicam tablets and other treatment options before deciding to use meloxicam tablets. Use the lowest effective dose for the shortest duration consistent with individual patient treatment goals (see WARNINGS).

Meloxicam tablets are indicated for relief of the signs and symptoms of osteoarthritis and rheumatoid arthritis.

CONTRAINDICATIONS

Meloxicam tablet is contraindicated in patients with known hypersensitivity to meloxicam.

Meloxicam tablets should not be given to patients who have experienced asthma, urticaria, or allergic-type reactions after taking aspirin or other NSAIDs. Severe, rarely fatal, anaphylactic-like reactions to NSAIDs have been reported in such patients (see WARNINGS, Anaphylactoid Reactions, and PRECAUTIONS, Pre-existing Asthma).

Meloxicam tablet is contraindicated for the treatment of peri-operative pain in the setting of coronary artery bypass graft (CABG) surgery (see WARNINGS).

WARNINGS

Cardiovascular Effects

Cardiovascular Thrombotic Events

Clinical trials of several COX-2 selective and nonselective NSAIDs of up to three years duration have shown an increased risk of serious cardiovascular (CV) thrombotic events, myocardial infarction, and stroke, which can be fatal. All NSAIDs, both COX-2 selective and nonselective, may have a similar risk. Patients with known CV disease or risk factors for CV disease may be at greater risk. To minimize the potential risk for an adverse CV event in patients treated with an NSAID, the lowest effective dose should be used for the shortest duration possible. Physicians and patients should remain alert for the development of such events, even in the absence of previous CV symptoms. Patients should be informed about the signs and/or symptoms of serious CV events and the steps to take if they occur.

There is no consistent evidence that concurrent use of aspirin mitigates the increased risk of serious CV thrombotic events associated with NSAID use. The concurrent use of aspirin and an NSAID does increase the risk of serious GI events (see WARNINGS, Gastrointestinal (GI) Effects - Risk of GI Ulceration, Bleeding, and Perforation).

Two large, controlled, clinical trials of a COX-2 selective NSAID for the treatment of pain in the first 10-14 days following CABG surgery found an increased incidence of myocardial infarction and stroke (see CONTRAINDICATIONS).

Hypertension

NSAIDs, including meloxicam tablets, can lead to onset of new hypertension or worsening of pre-existing hypertension, either of which may contribute to the increased incidence of CV events. Patients taking thiazides or loop diuretics may have impaired response to these therapies when taking NSAIDs. NSAIDs, including meloxicam tablets, should be used with caution in patients with hypertension. Blood pressure (BP) should be monitored closely during the initiation of NSAID treatment and throughout the course of therapy.

Congestive Heart Failure and Edema

Fluid retention and edema have been observed in some patients taking NSAIDs. Meloxicam tablets should be used with caution in patients with fluid retention, hypertension, or heart failure.

Gastrointestinal (GI) Effects - Risk of GI Ulceration, Bleeding, and Perforation

NSAIDs, including meloxicam tablets, can cause serious gastrointestinal (GI) adverse events including inflammation, bleeding, ulceration, and perforation of the stomach, small intestine, or large intestine, which can be fatal. These serious adverse events can occur at any time, with or without warning symptoms, in patients treated with NSAIDs. Only one in five patients, who develop a serious upper GI adverse event on NSAID therapy, is symptomatic. Upper GI ulcers, gross bleeding, or perforation caused by NSAIDs, occur in approximately 1% of patients treated for 3-6 months, and in about 2-4% of patients treated for one year. These trends continue with longer duration of use, increasing the likelihood of developing a serious GI event at some time during the course of therapy. However, even short-term therapy is not without risk.

NSAIDs should be prescribed with extreme caution in those with a prior history of ulcer disease or gastrointestinal bleeding. Patients with a prior history of peptic ulcer disease and/or gastrointestinal bleeding who use NSAIDs have a greater than 10 fold increased risk for developing a GI bleed compared to patients with neither of these risk factors. Other factors that increase the risk for GI bleeding in patients treated with NSAIDs include concomitant use of oral corticosteroids or anticoagulants, longer duration of NSAID therapy, smoking, use of alcohol, older age, and poor general health status. Most spontaneous reports of fatal GI events are in elderly or debilitated patients and therefore, special care should be taken in treating this population.

To minimize the potential risk for an adverse GI event in patients treated with an NSAID, the lowest effective dose should be used for the shortest possible duration. Patients and physicians should remain alert for signs and symptoms of GI ulceration and bleeding during NSAID therapy and promptly initiate additional evaluation and treatment if a serious GI adverse event is suspected. This should include discontinuation of the NSAID until a serious GI adverse event is ruled out. For high-risk patients, alternate therapies that do not involve NSAIDs should be considered.

Renal Effects

Long-term administration of NSAIDs, including meloxicam tablets, can result in renal papillary necrosis, renal insufficiency, acute renal failure, and other renal injury. Renal toxicity has also been seen in patients in whom renal prostaglandins have a compensatory role in the maintenance of renal perfusion. In these patients, administration of a nonsteroidal anti-inflammatory drug may cause a dose-dependent reduction in prostaglandin formation and, secondarily, in renal blood flow, which may precipitate overt renal decompensation. Patients at greatest risk of this reaction are those with impaired renal function, heart failure, liver dysfunction, those taking diuretics, ACE inhibitors, and angiotensin II receptor antagonists, and the elderly. Discontinuation of NSAID therapy is usually followed by recovery to the pretreatment state.

Advanced Renal Disease

No information is available from controlled clinical studies regarding the use of meloxicam tablets in patients with advanced renal disease. Therefore, treatment with meloxicam tablet is not recommended in these patients with advanced renal disease. If meloxicam tablets therapy must be initiated, close monitoring of the patient's renal function is advisable.

Anaphylactoid Reactions

As with other NSAIDS, anaphylactoid reactions have occurred in patients without known prior exposure to meloxicam tablets. Meloxicam tablets should not be given to patients with the aspirin triad. This symptom complex typically occurs in asthmatic patients who experience rhinitis with or without nasal polyps, or who exhibit severe, potentially fatal bronchospasm after taking aspirin or other NSAIDs (see CONTRAINDICATIONS and PRECAUTIONS, Pre-existing Asthma). Emergency help should be sought in cases where an anaphylactoid reaction occurs.

Skin Reactions

NSAIDs, including meloxicam tablets, can cause serious skin adverse events such as exfoliative dermatitis, Stevens-Johnson Syndrome (SJS), and toxic epidermal necrolysis (TEN), which can be fatal. These serious events may occur without warning. Patients should be informed about the signs and symptoms of serious skin manifestations and use of the drug should be discontinued at the first appearance of skin rash or any other sign of hypersensitivity.

Pregnancy

In late pregnancy, as with other NSAIDs, meloxicam tablets should be avoided because it may cause premature closure of the ductus arteriosus.

PRECAUTIONS

General

Meloxicam tablets cannot be expected to substitute for corticosteroids or to treat corticosteroid insufficiency. Abrupt discontinuation of corticosteroids may lead to disease exacerbation. Patients on prolonged corticosteroid therapy should have their therapy tapered slowly if a decision is made to discontinue corticosteroids.

The pharmacological activity of meloxicam tablets in reducing fever and inflammation may diminish the utility of these diagnostic signs in detecting complications of presumed noninfectious, painful conditions.

Hepatic Effects

Borderline elevations of one or more liver tests may occur in up to 15% of patients taking NSAIDs including meloxicam tablets. These laboratory abnormalities may progress, may remain unchanged, or may be transient with continuing therapy. Notable elevations of ALT or AST (approximately three or more times the upper limit of normal) have been reported in approximately 1% of patients in clinical trials with NSAIDs. In addition, rare cases of severe hepatic reactions, including jaundice and fatal fulminant hepatitis, liver necrosis and hepatic failure, some of them with fatal outcomes have been reported.

A patient with symptoms and/or signs suggesting liver dysfunction, or in whom an abnormal liver test has occurred, should be evaluated for evidence of the development of a more severe hepatic reaction while on therapy with meloxicam tablets. If clinical signs and symptoms consistent with liver disease develop, or if systemic manifestations occur (e.g., eosinophilia, rash, etc.), meloxicam tablets should be discontinued.

Renal Effects

Caution should be used when initiating treatment with meloxicam tablets in patients with considerable dehydration. It is advisable to rehydrate patients first and then start therapy with meloxicam tablets. Caution is also recommended in patients with pre-existing kidney disease (see WARNINGS, Renal Effects and Advanced Renal Disease).

The extent to which metabolites may accumulate in patients with renal failure has not been studied with meloxicam tablets. Because some meloxicam tablets metabolites are excreted by the kidney, patients with significantly impaired renal function should be more closely monitored.

Hematological Effects

Anemia is sometimes seen in patients receiving NSAIDs, including meloxicam tablets. This may be due to fluid retention, occult or gross GI blood loss, or an incompletely described effect upon erythropoiesis. Patients on long-term treatment with NSAIDs, including meloxicam tablets, should have their hemoglobin or hematocrit checked if they exhibit any signs or symptoms of anemia.

Drugs which inhibit the biosynthesis of prostaglandins may interfere to some extent with platelet function and vascular responses to bleeding.

NSAIDs inhibit platelet aggregation and have been shown to prolong bleeding time in some patients. Unlike aspirin their effect on platelet function is quantitatively less, of shorter duration, and reversible. Patients receiving meloxicam tablets who may be adversely affected by alterations in platelet function, such as those with coagulation disorders or patients receiving anticoagulants, should be carefully monitored.

Pre-existing Asthma

Patients with asthma may have aspirin-sensitive asthma. The use of aspirin in patients with aspirin-sensitive asthma has been associated with severe bronchospasm which can be fatal. Since cross reactivity, including bronchospasm, between aspirin and other NSAIDs has been reported in such aspirin-sensitive patients, meloxicam tablets should not be administered to patients with this form of aspirin sensitivity and should be used with caution in patients with pre-existing asthma.

Information for Patients

Patients should be informed of the following information before initiating therapy with an NSAID and periodically during the course of ongoing therapy. Patients should also be encouraged to read the NSAID Medication Guide that accompanies each prescription dispensed.

- Meloxicam tablets, like other NSAIDs, may cause serious CV side effects, such as MI or stroke, which may result in hospitalization and even death. Although serious CV events can occur without warning symptoms, patients should be alert for the signs and symptoms of chest pain, shortness of breath, weakness, slurring of speech, and should ask for medical advice when observing any indicative sign or symptoms. Patients should be apprised of the importance of this follow-up (see WARNINGS, Cardiovascular Effects).
- Meloxicam tablets, like other NSAIDs, can cause GI discomfort and, rarely, serious GI side effects, such as ulcers and bleeding, which may result in hospitalization and even death. Although serious GI tract ulcerations and bleeding can occur without warning symptoms, patients should be alert for the signs and symptoms of ulcerations and bleeding, and should ask for medical advice when observing any indicative sign or symptoms including epigastric pain, dyspepsia, melena, and hematemesis. Patients should be apprised of the importance of this follow-up (see WARNINGS, Gastrointestinal (GI) Effects - Risk of GI Ulceration, Bleeding, and Perforation).
- Meloxicam tablets, like other NSAIDs, can cause serious skin side effects such as exfoliative dermatitis, SJS, and TEN, which may result in hospitalizations and even death. Although serious skin reactions may occur without warning, patients should be alert for the signs and symptoms of skin rash and blisters, fever, or other signs of hypersensitivity such as itching, and should ask for medical advice when observing any indicative signs or symptoms. Patients should be advised to stop the drug immediately if they develop any type of rash and contact their physicians as soon as possible.
- Patients should promptly report signs or symptoms of unexplained weight gain or edema to their physicians.
- Patients should be informed of the warning signs and symptoms of hepatotoxicity (e.g., nausea, fatigue, lethargy, pruritus, jaundice, right upper quadrant tenderness, and "flu-like" symptoms). If these occur, patients should be instructed to stop therapy and seek immediate medical therapy.
- Patients should be informed of the signs of an anaphylactoid reaction (e.g., difficulty breathing, swelling of the face or throat). If these occur, patients should be instructed to seek immediate emergency help (see WARNINGS).
- In late pregnancy, as with other NSAIDs, meloxicam tablets should be avoided because it may cause premature closure of the ductus arteriosus.

Laboratory Tests

Because serious GI tract ulcerations and bleeding can occur without warning symptoms, physicians should monitor for signs or symptoms of GI bleeding. Patients on long-term treatment with NSAIDs should have their CBC and a chemistry profile checked periodically. If clinical signs and symptoms consistent with liver or renal disease develop, systemic manifestations occur (e.g., eosinophilia, rash, etc.) or if abnormal liver tests persist or worsen, meloxicam tablets should be discontinued.

Drug Interactions

ACE-inhibitors

Reports suggest that NSAIDs may diminish the antihypertensive effect of ACE-inhibitors. This interaction should be given consideration in patients taking NSAIDs concomitantly with ACE inhibitors.

Aspirin

When meloxicam tablet is administered with aspirin (1000 mg TID) to healthy volunteers, it tended to increase the AUC (10%) and Cmax (24%) of meloxicam. The clinical significance of this interaction is not known; however, as with other NSAIDs concomitant administration of meloxicam and aspirin is not generally recommended because of the potential for increased adverse effects.

Concomitant administration of low-dose aspirin with meloxicam tablets may result in an increased rate of GI ulceration or other complications, compared to use of meloxicam tablets alone. Meloxicam tablet is not a substitute for aspirin for cardiovascular prophylaxis.

Cholestyramine

Pretreatment for four days with cholestyramine significantly increased the clearance of meloxicam by 50%. This resulted in a decrease in t1/2, from 19.2 hours to 12.5 hours, and a 35% reduction in AUC. This suggests the existence of a recirculation pathway for meloxicam in the gastrointestinal tract. The clinical relevance of this interaction has not been established.

Cimetidine

Concomitant administration of 200 mg cimetidine QID did not alter the single-dose pharmacokinetics of 30 mg meloxicam.

Digoxin

Meloxicam 15 mg once daily for 7 days did not alter the plasma concentration profile of digoxin after ß-acetyldigoxin administration for 7 days at clinical doses. In vitro testing found no protein binding drug interaction between digoxin and meloxicam.

Furosemide

Clinical studies, as well as post-marketing observations, have shown that NSAIDs can reduce the natriuretic effect of furosemide and thiazides in some patients. This response has been attributed to inhibition of renal prostaglandin synthesis. Studies with furosemide agents and meloxicam have not demonstrated a reduction in natriuretic effect. Furosemide single and multiple dose pharmacodynamics and pharmacokinetics are not affected by multiple doses of meloxicam. Nevertheless, during concomitant therapy with meloxicam tablets, patients should be observed closely for signs of declining renal failure (see WARNINGS, Renal Effects), as well as to assure diuretic efficacy.

Lithium

In a study conducted in healthy subjects, mean pre-dose lithium concentration and AUC were increased by 21% in subjects receiving lithium doses ranging from 804 to 1072 mg BID with meloxicam 15 mg QD as compared to subjects receiving lithium alone. These effects have been attributed to inhibition of renal prostaglandin synthesis by meloxicam tablets. Patients on lithium treatment should be closely monitored for signs of lithium toxicity when meloxicam tablet is introduced, adjusted, or withdrawn.

Methotrexate

NSAIDs have been reported to competitively inhibit methotrexate accumulation in rabbit kidney slices. This may indicate that they could enhance the toxicity of methotrexate. Caution should be used when NSAIDs are administered concomitantly with methotrexate.

A study in 13 rheumatoid arthritis (RA) patients evaluated the effects of multiple doses of meloxicam on the pharmacokinetics of methotrexate taken once weekly. Meloxicam did not have a significant effect on the pharmacokinetics of single doses of methotrexate. In vitro, methotrexate did not displace meloxicam from its human serum binding sites.

Warfarin

The effects of warfarin and NSAIDs on GI bleeding are synergistic, such that users of both drugs together have a risk of serious GI bleeding higher than users of either drug alone.

Anticoagulant activity should be monitored, particularly in the first few days after initiating or changing meloxicam tablets therapy in patients receiving warfarin or similar agents, since these patients are at an increased risk of bleeding. The effect of meloxicam on the anticoagulant effect of warfarin was studied in a group of healthy subjects receiving daily doses of warfarin that produced an INR (International Normalized Ratio) between 1.2 and 1.8. In these subjects, meloxicam did not alter warfarin pharmacokinetics and the average anticoagulant effect of warfarin as determined by prothrombin time. However, one subject showed an increase in INR from 1.5 to 2.1. Caution should be used when administering meloxicam tablets with warfarin since patients on warfarin may experience changes in INR and an increased risk of bleeding complications when a new medication is introduced.

Carcinogenesis, Mutagenesis, Impairment of Fertility

No carcinogenic effect of meloxicam was observed in rats given oral doses up to 0.8 mg/kg/day (approximately 0.4-fold the human dose at 15 mg/day for a 50 kg adult based on body surface area conversion) for 104 weeks or in mice given oral doses up to 8.0 mg/kg/day (approximately 2.2-fold the human dose, as noted above) for 99 weeks.

Meloxicam was not mutagenic in an Ames assay, or clastogenic in a chromosome aberration assay with human lymphocytes and an in vivo micronucleus test in mouse bone marrow.

Meloxicam did not impair male and female fertility in rats at oral doses up to 9 and 5 mg/kg/day, respectively (4.9-fold and 2.5-fold the human dose, as noted above). However, an increased incidence of embryolethality at oral doses ≥ 1 mg/kg/day (0.5-fold the human dose, as noted above) was observed in rats when dams were given meloxicam 2 weeks prior to mating and during early embryonic development.

Pregnancy

Teratogenic Effects: Pregnancy Category C.

Meloxicam caused an increased incidence of septal defect of the heart, a rare event, at an oral dose of 60 mg/kg/day (64.5-fold the human dose at 15 mg/day for a 50 kg adult based on body surface area conversion) and embryolethality at oral doses ≥ 5 mg/kg/day (5.4-fold the human dose, as noted above) when rabbits were treated throughout organogenesis. Meloxicam was not teratogenic in rats up to an oral dose of 4 mg/kg/day (approximately 2.2-fold the human dose, as noted above) throughout organogenesis. An increased incidence of stillbirths was observed when rats were given oral doses ≥ 1 mg/kg/day throughout organogenesis. Meloxicam crosses the placental barrier. There are no adequate and well-controlled studies in pregnant women. Meloxicam tablets should be used during pregnancy only if the potential benefit justifies the potential risk to the fetus.

Nonteratogenic Effects

Because of the known effects of nonsteroidal anti-inflammatory drugs on the fetal cardiovascular system (closure of ductus arteriosus), use during pregnancy (particularly late pregnancy) should be avoided.

Meloxicam caused a reduction in birth index, live births, and neonatal survival at oral doses ≥ 0.125 mg/kg/day (approximately 0.07-fold the human dose at 15 mg/day for a 50 kg adult based on body surface area conversion) when rats were treated during the late gestation and lactation period. No studies have been conducted to evaluate the effect of meloxicam on the closure of the ductus arteriosus in humans; use of meloxicam during the third trimester of pregnancy should be avoided.

Labor and Delivery

Studies in rats with meloxicam, as with other drugs known to inhibit prostaglandin synthesis, showed an increased incidence of stillbirths, prolonged delivery, and delayed parturition at oral dosages ≥1 mg/kg/day (approximately 0.5-fold the human dose at 15 mg/day for a 50 kg adult based on body surface area conversion), and decreased pup survival at an oral dose of 4 mg/kg/day (approximately 2.1-fold the human dose, as noted above) throughout organogenesis. Similar findings were observed in rats receiving oral dosages ≥ 0.125 mg/kg/day (approximately 0.07-fold the human dose, as noted above) during late gestation and the lactation period.

The effects of meloxicam tablets on labor and delivery in pregnant women are unknown.

Nursing Mothers

It is not known whether this drug is excreted in human milk however, meloxicam was excreted in the milk of lactating rats at concentrations higher than those in plasma. Because many drugs are excreted in human milk and because of the potential for serious adverse reactions in nursing infants from meloxicam tablets, a decision should be made whether to discontinue nursing or to discontinue the drug, taking into account the importance of the drug to the mother.

Pediatric Use

Use of this drug for a pediatric indication is protected by marketing exclusivity.

Geriatric Use

As with any NSAID, caution should be exercised in treating the elderly (65 years and older).

ADVERSE REACTIONS

Adults

Osteoarthritis and Rheumatoid Arthritis

The meloxicam Phase 2/3 clinical trial database includes 10,122 OA patients and 1012 RA patients treated with meloxicam 7.5 mg/day, 3,505 OA patients and 1351 RA patients treated with meloxicam 15 mg/day. Meloxicam at these doses was administered to 661 patients for at least 6 months and to 312 patients for at least one year. Approximately 10,500 of these patients were treated in ten placebo and/or active-controlled osteoarthritis trials and 2363 of these patients were treated in ten placebo and/or active-controlled rheumatoid arthritis trials. Gastrointestinal (GI) adverse events were the most frequently reported adverse events in all treatment groups across meloxicam trials.

A 12-week multicenter, double-blind, randomized trial was conducted in patients with osteoarthritis of the knee or hip to compare the efficacy and safety of meloxicam with placebo and with an active control. Two 12-week multicenter, double-blind, randomized trials were conducted in patients with rheumatoid arthritis to compare the efficacy and safety of meloxicam with placebo.

Table 2a depicts adverse events that occurred in ≥ 2% of the meloxicam treatment groups in a 12-week placebo and active-controlled osteoarthritis trial.

Table 2b depicts adverse events that occurred in ≥ 2% of the meloxicam treatment groups in two 12-week placebo controlled rheumatoid arthritis trials.

Table 2a Adverse Events (%) Occurring in ≥ 2% of Meloxicam Patients in a 12-Week Osteoarthritis Placebo and Active-Controlled Trial
 | Placebo | Meloxicam 7.5 mg daily | Meloxicam 15 mg daily | Diclofenac 100 mg daily
No. of Patients | 157 | 154 | 156 | 153
Gastrointestinal | 17.2 | 20.1 | 17.3 | 28.1
Abdominal Pain | 2.5 | 1.9 | 2.6 | 1.3
Diarrhea | 3.8 | 7.8 | 3.2 | 9.2
Dyspepsia | 4.5 | 4.5 | 4.5 | 6.5
Flatulence | 4.5 | 3.2 | 3.2 | 3.9
Nausea | 3.2 | 3.9 | 3.8 | 7.2
Body as a Whole
Accident Household | 1.9 | 4.5 | 3.2 | 2.6
Edema^1 | 2.5 | 1.9 | 4.5 | 3.3
Fall | 0.6 | 2.6 | 0.0 | 1.3
Influenza-Like Symptoms | 5.1 | 4.5 | 5.8 | 2.6
Central and Peripheral Nervous System
Dizziness | 3.2 | 2.6 | 3.8 | 2.0
Headache | 10.2 | 7.8 | 8.3 | 5.9
Respiratory
Pharyngitis | 1.3 | 0.6 | 3.2 | 1.3
Upper Respiratory Tract Infection | 1.9 | 3.2 | 1.9 | 3.3
Skin
Rash^2 | 2.5 | 2.6 | 0.6 | 2.0
^1 WHO preferred terms edema, edema dependent, edema peripheral and edema legs combined
^2 WHO preferred terms rash, rash erythematous and rash maculo-papular combined

Table 2b Adverse Events (%) Occurring in ≥ 2% of Meloxicam Patients in two 12-Week Rheumatoid Arthritis Placebo Controlled Trials
 | Placebo | Meloxicam 7.5 mg daily | Meloxicam 15 mg daily
No. of Patients | 469 | 481 | 477
Gastrointestinal disorders Abdominal pain NOS^2 Diarrhea NOS^2 Dyspeptic signs and symptoms^1 Nausea^2 | 14.1 0.6 5.1 3.8 2.6 | 18.9 2.9 4.8 5.8 3.3 | 16.8 2.3 3.4 4.0 3.8
General disorders and administration site conditions Influenza like illness^2 | 2.1 | 2.9 | 2.3
Infection and infestations Upper respiratory tract infections pathogen class unspecified^2 | 4.1 | 7.0 | 6.5
Musculoskeletal and connective tissue disorders Joint related signs and symptoms^1 Musculoskeletal and connective tissue signs and symptoms NEC^1 | 1.9 3.8 | 1.5 1.7 | 2.3 2.9
Nervous system disorders Headaches NOS^2 Dizziness (excl vertigo)^2 | 6.4 3.0 | 6.4 2.3 | 5.5 0.4
Skin and subcutaneous tissue disorders Rash NOS^2 | 1.7 | 1.0 | 2.1
^1MedDRA high level term (preferred terms): dyspeptic signs and symptoms (dyspepsia, dyspepsia aggravated, eructation, gastrointestinal irritation), upper respiratory tract infections-pathogen unspecified (laryngitis NOS, pharyngitis NOS, sinusitis NOS), joint related signs and symptoms (arthralgia, arthralgia aggravated, joint crepitation, joint effusion, joint swelling), and musculoskeletal and connective tissue signs and symptoms NEC (back pain, back pain aggravated, muscle spasms, musculoskeletal pain)
^2MedDRA preferred term: diarrhea NOS, nausea, abdominal pain NOS, influenza like illness, headaches NOS, dizziness (excl vertigo), and rash NOS

The adverse events that occurred with meloxicam in ≥ 2% of patients treated short-term (4-6 weeks) and long-term (6 months) in active-controlled osteoarthritis trials are presented in Table 3.

Table 3 Adverse Events (%) Occurring in ≥ 2% of Meloxicam Patients in 4 to 6 Weeks and 6 Month Active-Controlled Osteoarthritis Trials
 | 4-6 Weeks Controlled Trials |  | 6 Month Controlled Trials
 | Meloxicam 7.5 mg daily | Meloxicam 15 mg daily | Meloxicam 7.5 mg daily | Meloxicam 15 mg daily
No. of Patients | 8955 | 256 | 169 | 306
Gastrointestinal | 11.8 | 18.0 | 26.6 | 24.2
Abdominal Pain | 2.7 | 2.3 | 4.7 | 2.9
Constipation | 0.8 | 1.2 | 1.8 | 2.6
Diarrhea | 1.9 | 2.7 | 5.9 | 2.6
Dyspepsia | 3.8 | 7.4 | 8.9 | 9.5
Flatulence | 0.5 | 0.4 | 3.0 | 2.6
Nausea | 2.4 | 4.7 | 4.7 | 7.2
Vomiting | 0.6 | 0.8 | 1.8 | 2.6
Body as a Whole
Accident Household | 0.0 | 0.0 | 0.6 | 2.9
Edema^1 | 0.6 | 2.0 | 2.4 | 1.6
Pain | 0.9 | 2.0 | 3.6 | 5.2
Central and Peripheral Nervous System
Dizziness | 1.1 | 1.6 | 2.4 | 2.6
Headache | 2.4 | 2.7 | 3.6 | 2.6
Hematologic
Anemia | 0.1 | 0.0 | 4.1 | 2.9
Musculoskeletal
Arthralgia | 0.5 | 0.0 | 5.3 | 1.3
Back Pain | 0.5 | 0.4 | 3.0 | 0.7
Psychiatric Disorders
Insomnia | 0.4 | 0.0 | 3.6 | 1.6
Respiratory
Coughing | 0.2 | 0.8 | 2.4 | 1.0
Upper Respiratory Tract Infection | 0.2 | 0.0 | 8.3 | 7.5
Skin
Pruritus | 0.4 | 1.2 | 2.4 | 0.0
Rash^2 | 0.3 | 1.2 | 3.0 | 1.3
Urinary
Micturition Frequency | 0.1 | 0.4 | 2.4 | 1.3
Urinary Tract Infection | 0.3 | 0.4 | 4.7 | 6.9
^1 WHO preferred terms edema, edema dependent, edema peripheral and edema legs combined
^2 WHO preferred terms rash, rash erythematous and rash maculo-papular combined

Higher doses of meloxicam (22.5 mg and greater) have been associated with an increased risk of serious GI events; therefore the daily dose of meloxicam should not exceed 15 mg.

The following is a list of adverse drug reactions occurring in < 2% of patients receiving meloxicam in clinical trials involving approximately 16,200 patients. Adverse reactions reported only in worldwide postmarketing experience or the literature are shown in italics

Body as a Whole | allergic reaction, anaphylactoid reactions including shock, face edema, fatigue, fever, hot flushes, malaise, syncope, weight decrease, weight increase
Cardiovascular | angina pectoris, cardiac failure, hypertension, hypotension, myocardial infarction, vasculitis
Central and Peripheral Nervous System | convulsions, paresthesia, tremor, vertigo
Gastrointestinal | colitis, dry mouth, duodenal ulcer, eructation, esophagitis, gastric ulcer, gastritis, gastroesophageal reflux, gastrointestinal hemorrhage, hematemesis, hemorrhagic duodenal ulcer, hemorrhagic gastric ulcer, intestinal perforation, melena, pancreatitis, perforated duodenal ulcer, perforated gastric ulcer, stomatitis ulcerative
Heart Rate and Rhythm | arrhythmia, palpitation, tachycardia
Hematologic | agranulocytosis, leukopenia, purpura, thrombocytopenia
Liver and Biliary System | ALT increased, AST increased, bilirubinemia, GGT increased, hepatitis, jaundice, liver failure
Metabolic and Nutritional | dehydration
Psychiatric | abnormal dreaming, alterations in mood (such as mood elevation), anxiety, appetite increased, confusion, depression,nervousness, somnolence
Respiratory | asthma, bronchospasm, dyspnea
Skin and Appendages | alopecia, angioedema, bullous eruption, erythema multiforme, photosensitivity reaction, pruritus, exfoliative dermatitis, Stevens-Johnson syndrome, sweating increased, toxic epidermal necrolysis, urticaria
Special Senses | abnormal vision, conjunctivitis, taste perversion, tinnitus
Urinary System | acute urinary retention, albuminuria, BUN increased, creatinine increased, hematuria, interstitial nephritis, renal failure

OVERDOSAGE

There is limited experience with meloxicam overdose. Four cases have taken 6 to 11 times the highest recommended dose; all recovered. Cholestyramine is known to accelerate the clearance of meloxicam.

Symptoms following acute NSAID overdose are usually limited to lethargy, drowsiness, nausea, vomiting, and epigastric pain, which are generally reversible with supportive care. Gastrointestinal bleeding can occur. Severe poisoning may result in hypertension, acute renal failure, hepatic dysfunction, respiratory depression, coma, convulsions, cardiovascular collapse, and cardiac arrest. Anaphylactoid reactions have been reported with therapeutic ingestion of NSAIDs, and may occur following an overdose.

Patients should be managed with symptomatic and supportive care following an NSAID overdose. In cases of acute overdose, gastric lavage followed by activated charcoal is recommended. Gastric lavage performed more than one hour after overdose has little benefit in the treatment of overdose. Administration of activated charcoal is recommended for patients who present 1-2 hours after overdose. For substantial overdose or severely symptomatic patients, activated charcoal may be administered repeatedly. Accelerated removal of meloxicam by 4 gm oral doses of cholestyramine given three times a day was demonstrated in a clinical trial. Administration of cholestyramine may be useful following an overdose. Forced diuresis, alkalinization of urine, hemodialysis, or hemoperfusion may not be useful due to high protein binding.

DOSAGE AND ADMINISTRATION

Osteoarthritis and Rheumatoid Arthritis

Carefully consider the potential benefits and risks of meloxicam tablets and other treatment options before deciding to use meloxicam tablets. Use the lowest effective dose for the shortest duration consistent with individual patient treatment goals (see WARNINGS).

After observing the response to initial therapy with meloxicam tablets, the dose should be adjusted to suit an individual patient's needs.

For the relief of the signs and symptoms of osteoarthritis the recommended starting and maintenance oral dose of meloxicam is 7.5 mg once daily. Some patients may receive additional benefit by increasing the dose to 15 mg once daily. For the relief of the signs and symptoms of rheumatoid arthritis, the recommended starting and maintenance oral dose of meloxicam is 7.5 mg once daily. Some patients may receive additional benefit by increasing the dose to 15 mg once daily.

The maximum recommended daily oral dose of meloxicam is 15 mg regardless of formulation.

Meloxicam may be taken without regard to timing of meals.

HOW SUPPLIED

Meloxicam Tablets, 7.5 mg, yellow colored, circular, biconvex tablets, debossed with “512” on one side and plain on the other side are available as follows:

Bottle of 30 NDC 42549-604-30
Bottle of 60 NDC 42549-604-60
Bottle of 90 NDC 42549-604-90
Bottle of 120 NDC 42549-604-12

Meloxicam Tablets, 15 mg, yellow colored, oval, biconvex tablets, debossed with “513” on one side and plain on the other side are available as follows:

Bottle of 30 NDC 42549-519-30
Bottle of 60 NDC 42549-519-60
Bottle of 90 NDC 42549-519-90
Bottle of 120 NDC 42549-519-12

Store at 25ºC (77ºF); excursions permitted to 15ºC-30ºC (59ºF-86ºF). Keep Meloxicam tablets in a dry place.

Dispense tablets in a tight container.

Keep this and all medications out of the reach of children.

Manufactured by:
Caraco Pharmaceutical Laboratories, Ltd.
1150 Elijah McCoy Drive
Detroit, MI 48202

C.S.No. 5481T05

Medication Guide for Non-Steroidal Anti-Inflammatory Drugs (NSAIDs)

(See the end of this Medication Guide for a list of prescription NSAID medicines).

What is the most important information I should know about medicines called Non-Steroidal Anti-Inflammatory Drugs (NSAIDs)?

NSAID medicines may increase the chance of a heart attack or stroke that can lead to death. This chance increases:

- with longer use of NSAID medicines
- in people who have heart disease

NSAID medicines should never be used right before or after a heart surgery called a “coronary artery bypass graft (CABG).”

NSAID medicines can cause ulcers and bleeding in the stomach and intestines at any time during treatment. Ulcers and bleeding:

- can happen without warning symptoms
- may cause death

The chance of a person getting an ulcer or bleeding increases with:

- taking medicines called “corticosteroids” and “anticoagulants”
- longer use
- smoking
- drinking alcohol
- older age
- having poor health

NSAID medicines should only be used:

- exactly as prescribed
- at the lowest dose possible for your treatment
- for the shortest time needed

What are Non-Steroidal Anti-Inflammatory Drugs (NSAIDs)?

NSAID medicines are used to treat pain and redness, swelling, and heat (inflammation) from medical conditions such as:

- different types of arthritis
- menstrual cramps and other types of short-term pain

Who should not take a Non-Steroidal Anti-Inflammatory Drug (NSAID)?

Do not take an NSAID medicine:

- if you had an asthma attack, hives, or other allergic reaction with aspirin or any other NSAID medicine
- for pain right before or after heart bypass surgery

Tell your healthcare provider:

- about all of your medical conditions
- about all of the medicines you take. NSAIDs and some other medicines can interact with each other and cause serious side effects. Keep a list of your medicines to show to your healthcare provider and pharmacist
- if you are pregnant. NSAID medicines should not be used by pregnant women late in their pregnancy
- if you are breastfeeding. Talk to your doctor

What are the possible side effects of Non-Steroidal Anti-Inflammatory Drugs (NSAIDs)?

Serious side effects include:

- heart attack
- stroke
- high blood pressure
- heart failure from body swelling (fluid retention)
- kidney problems including kidney failure
- bleeding and ulcers in the stomach and intestine
- low red blood cells (anemia)
- life-threatening skin reactions
- life-threatening allergic reactions
- liver problems including liver failure
- asthma attacks in people who have asthma

Other side effects include:

- stomach pain
- constipation
- diarrhea
- gas
- heartburn
- nausea
- Vomiting
- dizziness

Get emergency help right away if you have any of the following symptoms:

- shortness of breath or trouble breathing
- chest pain
- weakness in one part or side of your body
- slurred speech
- swelling of the face or throat

Stop your NSAID medicine and call your healthcare provider right away if you have any of the following symptoms:

- nausea
- more tired or weaker than usual
- itching
- your skin or eyes look yellow
- stomach pain
- flu-like symptoms
- vomit blood
- there is blood in your bowel movement or it is black and sticky like tar
- unusual weight gain
- skin rash or blisters with fever
- swelling of the arms and legs, hands and feet

These are not all the side effects with NSAID medicines. Talk to your healthcare provider or pharmacist for more information about NSAID medicines.

Other information about Non-Steroidal Anti-Inflammatory Drugs (NSAIDs):

- Aspirin is an NSAID medicine but it does not increase the chance of a heart attack. Aspirin can cause bleeding in the brain, stomach, and intestines. Aspirin can also cause ulcers in the stomach and intestines.
- Some of these NSAID medicines are sold in lower doses without a prescription (over-the counter). Talk to your healthcare provider before using over-the-counter NSAIDs for more than 10 days.

NSAID medicines that need a prescription

Generic Name | Product Trademark(s)
Celecoxib | Celebrex®
Diclofenac | Cataflam®, Voltaren®, Arthrotec™ (combined with misoprostol)
Diflunisal | Dolobid®
Etodolac | Lodine®, Lodine® XL
Fenoprofen | Nalfon®, Nalfon® 200
Flurbiprofen | Ansaid®
Ibuprofen | Motrin®, Tab-Profen®, Vicoprofen®* (combined with hydrocodone), combunox™ (combined with oxycodone)
Indomethacin | Indocin®, Indocin® SR, Indo-Lemmon™, Indomethegan™
Ketoprofen | Oruvail®
Ketorolac | Toradol®
Mefenamic | Acid Ponstel®
Meloxicam | Mobic®
Nabumetone | Relafen®
Naproxen | Naprosyn®, Anaprox®, Anaprox® DS, EC-Naprosyn™, Naprelan®, PREVACID, NapraPAC® (copackaged with lansoprazole)
Oxaprozin | Daypro®
Piroxicam | Feldene®
Sulindac | Clinoril®
Tolmetin | Tolectin®, Tolectin DS®, Tolectin® 600

All registered trademarks in this document are the property of their respective owners.

* Vicoprofen contains the same dose of ibuprofen as over-the-counter (OTC) NSAIDs, and is usually use for less than 10 days to treat pain. The OTC NSAID label warns that long term continuous use may increase the risk of heart attack or stroke.

Call your doctor for medical advice about side effects. You may report side effects to FDA at 1-800-FDA-1088.

This Medication Guide has been approved by the US Food and Drug Administration.

Manufactured by:
Caraco Pharmaceutical Laboratories, Ltd.
1150 Elijah McCoy Drive
Detroit, MI 48202

Relabeling and Repackaging by:
STAT Rx USA LLC
Gainesville, GA 30501

PRINCIPAL DISPLAY PANEL

Meloxicam 7.5 mg tablet(s)
RX Only

PRINCIPAL DISPLAY PANEL

Meloxicam 15 mg tablet(s)
RX Only